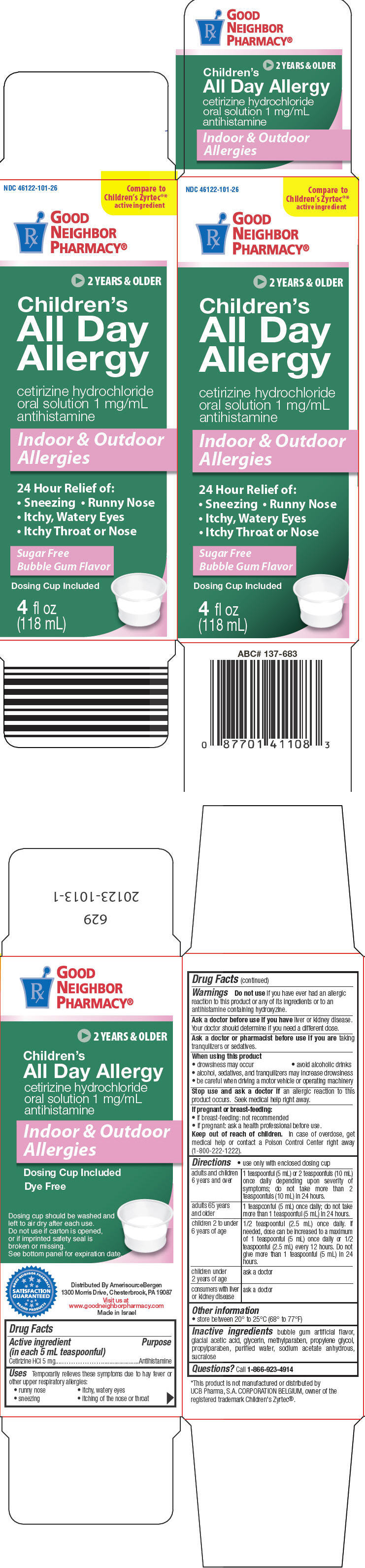 DRUG LABEL: All Day 
NDC: 46122-101 | Form: SOLUTION
Manufacturer: Amerisource Bergen
Category: otc | Type: HUMAN OTC DRUG LABEL
Date: 20200618

ACTIVE INGREDIENTS: Cetirizine Hydrochloride 5 mg/5 mL
INACTIVE INGREDIENTS: acetic acid; glycerin; methylparaben; propylene glycol; propylparaben; water; sodium acetate anhydrous; sucralose

All Day
Allergy

Drug Facts

Active ingredient (in each 5 mL teaspoonful)

Cetirizine HCl 5 mg

Purpose

Antihistamine

Uses

Temporarily relieves these symptoms due to hay fever or other upper respiratory allergies:

- runny nose
- itchy, watery eyes
- sneezing
- itching of the nose or throat

Warnings

Do not use if you have ever had an allergic reaction to this product or any of its ingredients or to an antihistamine containing hydroxyzine.

Ask a doctor before use if you have liver or kidney disease. Your doctor should determine if you need a different dose.

Ask a doctor or pharmacist before use if you are taking tranquilizers or sedatives.

When using this product

- drowsiness may occur
- avoid alcoholic drinks
- alcohol, sedatives, and tranquilizers may increase drowsiness
- be careful when driving a motor vehicle or operating machinery

Stop use and ask a doctor if an allergic reaction to this product occurs. Seek medical help right away.

If pregnant or breast-feeding:

- if breast-feeding: not recommended
- if pregnant: ask a health professional before use.

Keep out of reach of children. In case of overdose, get medical help or contact a Poison Control Center right away (1-800-222-1222).

Directions

- use only with enclosed dosing cup

adults and children 6 years and over | 1 teaspoonful (5 mL) or 2 teaspoonfuls (10 mL) once daily depending upon severity of symptoms; do not take more than 2 teaspoonfuls (10 mL) in 24 hours.
adults 65 years and older | 1 teaspoonful (5 mL) once daily; do not take more than 1 teaspoonful (5 mL) in 24 hours.
children 2 to under 6 years of age | 1/2 teaspoonful (2.5 mL) once daily. If needed, dose can be increased to a maximum of 1 teaspoonful (5 mL) once daily or 1/2 teaspoonful (2.5 mL) every 12 hours. Do not give more than 1 teaspoonful (5 mL) in 24 hours.
children under 2 years of age | ask a doctor
consumers with liver or kidney disease | ask a doctor

Other information

- store between 20° to 25°C (68° to 77°F)

Inactive ingredients

bubble gum artificial flavor, glacial acetic acid, glycerin, methylparaben, propylene glycol, propylparaben, purified water, sodium acetate anhydrous, sucralose

Questions?

Call 1-866-923-4914

Distributed By AmerisourceBergen
1300 Morris Drive, Chesterbrook, PA 19087

PRINCIPAL DISPLAY PANEL - 118 mL Bottle Carton

NDC 46122-101-26

Compare to
Children's Zyrtec®*
active ingredient

Rx
GOOD
NEIGHBOR
PHARMACY®

2 YEARS & OLDER

Children's
All Day
Allergy

cetirizine hydrochloride
oral solution 1 mg/mL
antihistamine

Indoor & Outdoor
Allergies

24 Hour Relief of:

- Sneezing • Runny Nose
- Itchy, Watery Eyes
- Itchy Throat or Nose

Sugar Free
Bubble Gum Flavor

Dosing Cup Included

4 fl oz
(118 mL)